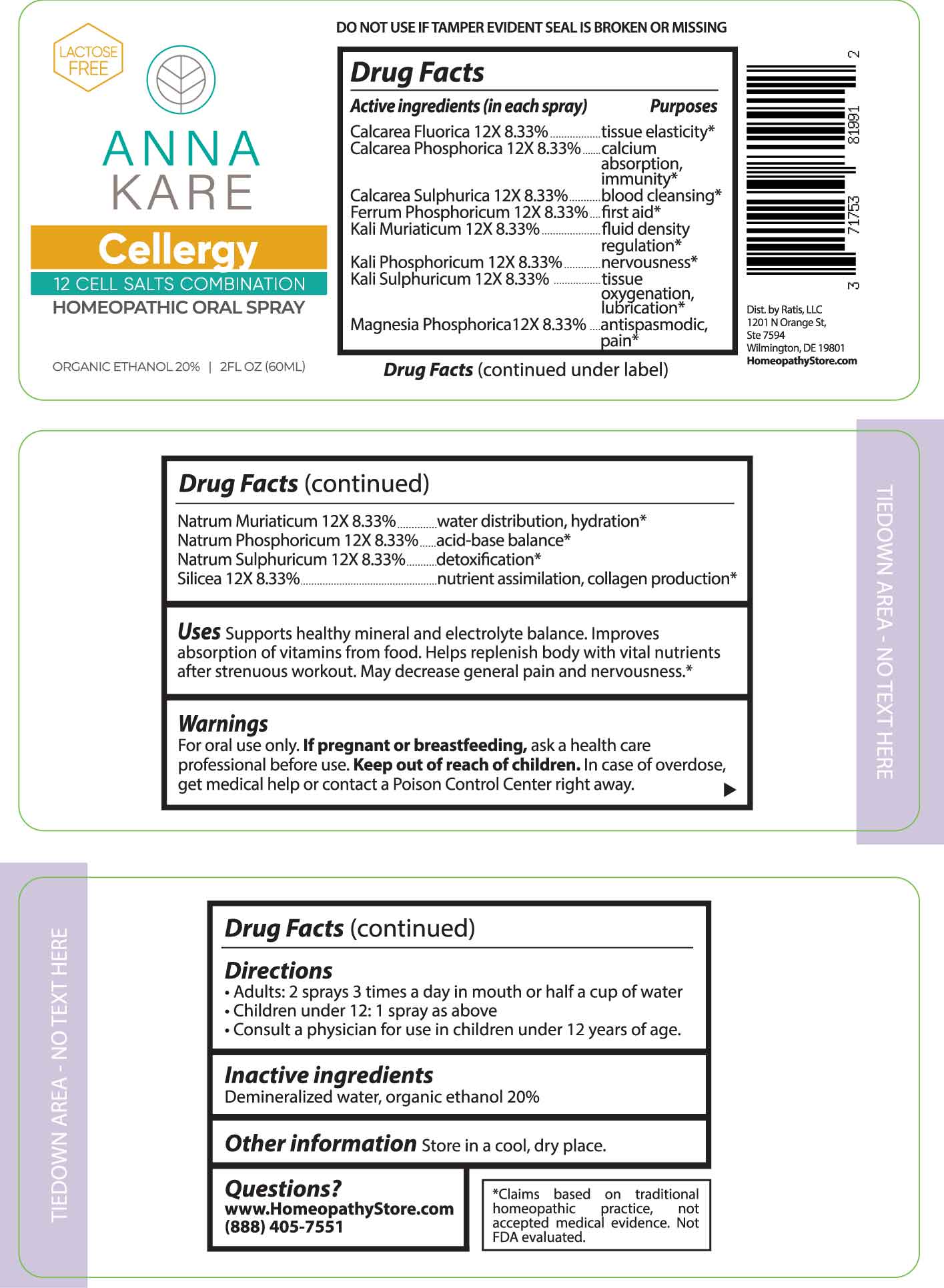 DRUG LABEL: Cellergy
NDC: 71753-8199 | Form: SPRAY
Manufacturer: Ratis, LLC
Category: homeopathic | Type: HUMAN OTC DRUG LABEL
Date: 20230807

ACTIVE INGREDIENTS: CALCIUM FLUORIDE 12 [hp_X]/1 mL; TRIBASIC CALCIUM PHOSPHATE 12 [hp_X]/1 mL; CALCIUM SULFATE ANHYDROUS 12 [hp_X]/1 mL; FERROSOFERRIC PHOSPHATE 12 [hp_X]/1 mL; POTASSIUM CHLORIDE 12 [hp_X]/1 mL; DIBASIC POTASSIUM PHOSPHATE 12 [hp_X]/1 mL; POTASSIUM SULFATE 12 [hp_X]/1 mL; MAGNESIUM PHOSPHATE, DIBASIC TRIHYDRATE 12 [hp_X]/1 mL; SODIUM CHLORIDE 12 [hp_X]/1 mL; SODIUM PHOSPHATE, DIBASIC, HEPTAHYDRATE 12 [hp_X]/1 mL; SODIUM SULFATE 12 [hp_X]/1 mL; SILICON DIOXIDE 12 [hp_X]/1 mL
INACTIVE INGREDIENTS: WATER; ALCOHOL

DRUG FACTS:

ACTIVE INGREDIENTS:

(in each spray) Calcarea Fluorica 12X 8.33%, Calcarea Phosphorica 12X 8.33%, Calcarea Sulphurica 12X 8.33%, Ferrum Phosphoricum 12X 8.33%, Kali Muriaticum 12X 8.33%, Kali Phosphoricum 12X 8.33%, Kali Sulphuricum 12X 8.33%, Magnesia Phosphorica 12X 8.33%, Natrum Muriaticum 12X 8.33%, Natrum Phosphoricum 12X 8.33%, Natrum Sulphuricum 12X 8.33%, Silicea 12X 8.33%.

PURPOSES:

Calcarea Fluorica - tissue elasticity,* Calcarea Phosphorica – calcium absorption, Immunity,* Calcarea Sulphurica – blood cleansing,* Ferrum Phosphoricum – first aid,* Kali Muriaticum – fluid density regulation,* Kali Phosphoricum - nervousness,* Kali Sulphuricum – tissue oxygenation, lubrication,* Magnesia Phosphorica – antispasmodic, pain,* Natrum Muriaticum – water distribution, hydration,* Natrum Phosphoricum – acid-base balance,* Natrum Sulphuricum - detoxification,* Silicea – nutrient assimilation, collagen production.*

USES:

Supports healthy mineral and electrolyte balance. Improves absorption of vitamins from food. Helps replenish body with vital nutrients after strenuous workout. May decrease general pain and nervousness.*

*Claims based on traditional homeopathic practice, not accepted medical evidence. Not FDA evaluated.

WARNINGS:

For oral use only.

If pregnant or breast-feeding, ask a health care professional before use.

Keep out of reach of children. In case of overdose, get medical help or contact a Poison Control center right away.

DO NOT USE IF TAMPER EVIDENT SEAL IS BROKEN OR MISSING

Store in a cool, dry place.

KEEP OUT OF REACH OF CHILDREN:

In case of overdose, get medical help or contact a Poison Control center right away.

DIRECTIONS:

• Adults: 2 sprays 3 times a day in mouth or half a cup of water

• Children under 12: 1 spay as above

• Consult a physician for use in children under 12 years of age.

INACTIVE INGREDIENTS:

Demineralized water, organic ethanol 20%

QUESTIONS:

Dist. by: Ratis, LLC

1201 N Orange St,

Ste7594

Wilmington, De 19801

www.HomeopathyStore.com

(888) 405-7551

PACKAGE LABLE DISPLAY:

LACTOSE FREE

ANNA

KARE

Cellergy

12 CELL SALTS COMBINATION

HOMEOPATHIC ORAL SPRAY

2FL OZ (60ML)